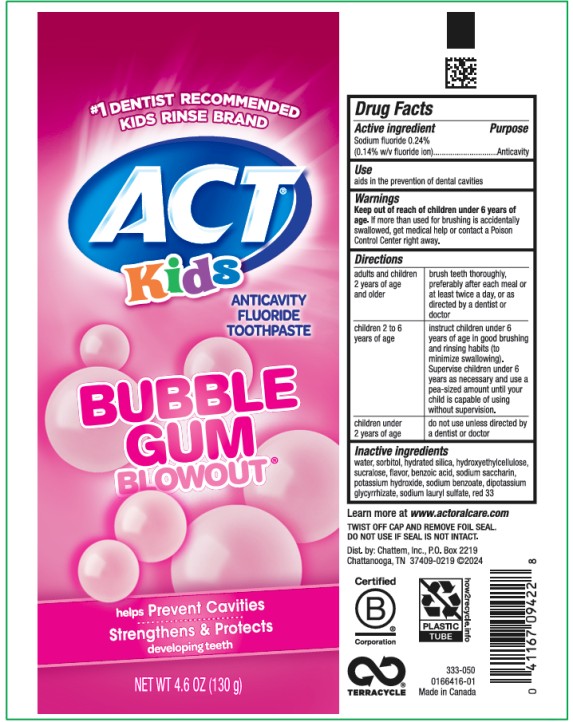 DRUG LABEL: ACT Kids Anticavity Fluoride
NDC: 41167-0922 | Form: PASTE
Manufacturer: Chattem, Inc.
Category: otc | Type: HUMAN OTC DRUG LABEL
Date: 20241201

ACTIVE INGREDIENTS: SODIUM FLUORIDE 1.4 mg/1 g
INACTIVE INGREDIENTS: WATER; SORBITOL; HYDRATED SILICA; HYDROXYETHYL CELLULOSE (1500 MPA.S AT 1%); SUCRALOSE; BENZOIC ACID; SACCHARIN SODIUM; POTASSIUM HYDROXIDE; SODIUM BENZOATE; GLYCYRRHIZINATE DIPOTASSIUM; SODIUM LAURYL SULFATE; D&C RED NO. 33

ACT Kids Toothpaste Bubblegum Blowout

ACT® Kids

Anticavity Fluoride Toothpaste

Bubblegum Blowout

Drug Facts

Active ingredient

Sodium fluoride 0.24% (0.14% w/v fluoride ion)

Purpose

Anticavity

Use

aids in the prevention of dental cavities

Warnings

Keep out of reach of children under 6 years of age.

If more than used for brushing is accidentally swallowed, get medical help or contact a Poison Control Center right away.

Directions

- adults and children 2 years of age and older: brush teeth thoroughly, preferably after each meal or at least twice a day, or as directed by a dentist or doctor.
- Children 2 to 6 years of age: instruct children under 6 years of age in good brushing and rinsing habits (to minimize swallowing). Supervise children under 6 as necessary and use a pea-sized amount until your child is capable of using without supervision.
- children under 2 years of age: do not use unless directed by a dentist or doctor

Inactive ingredients

water, sorbitol, hydrated silica, hydroxyethylcellulose, sucralose, flavor, benzoic acid, sodium saccharin, potassium hydroxide, sodium benzoate, dipotassium glycyrrhizate, sodium lauryl sulfate, red 33

PRINCIPAL DISPLAY PANEL

ACT
Kids
BUBBLE
GUM
BLOWOUT
NET WT 4.6 oz (130 g)